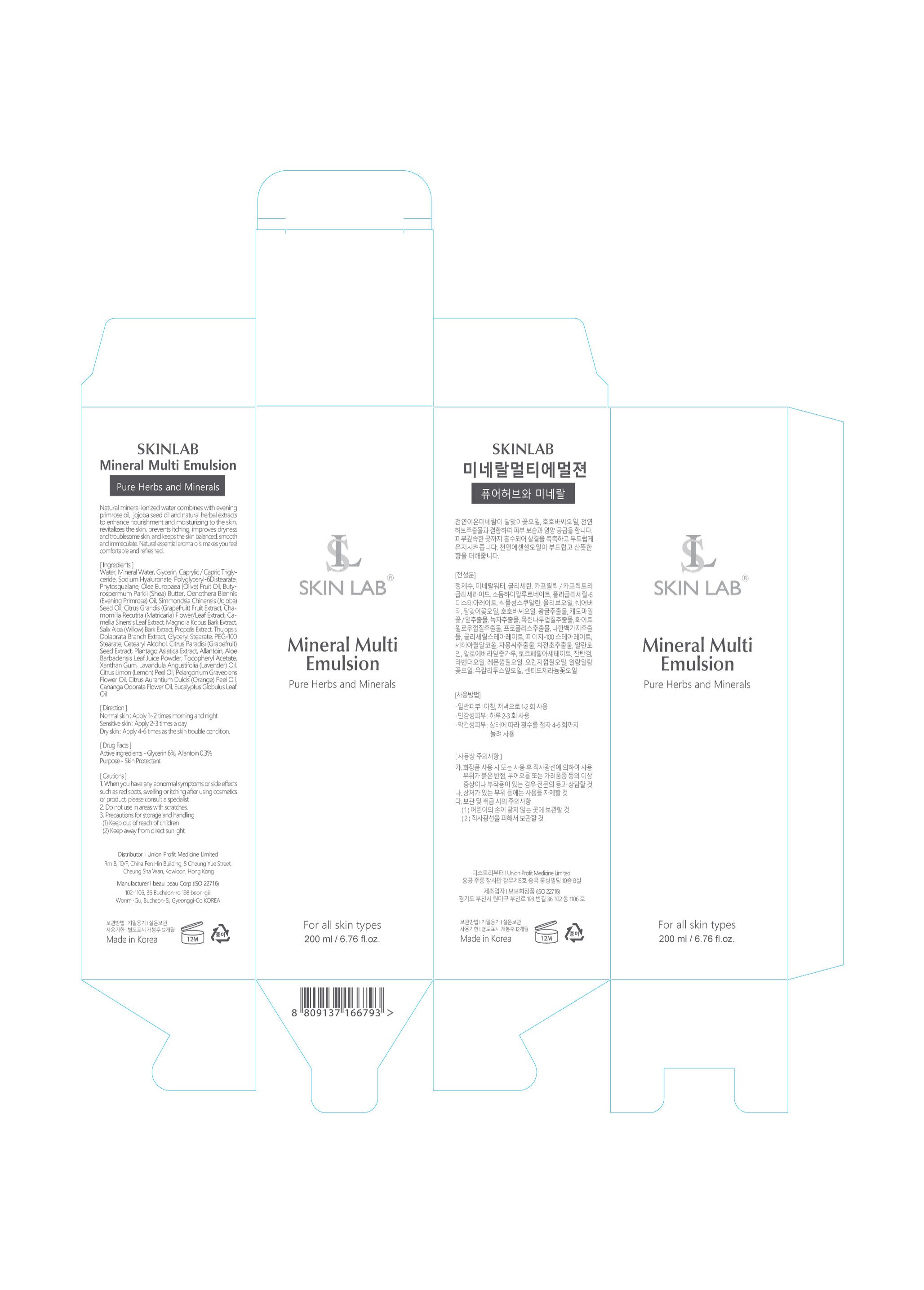 DRUG LABEL: Mineral Multi Emulsion
NDC: 73101-003 | Form: LIQUID
Manufacturer: UNION PROFIT MEDICINE LIMITED
Category: otc | Type: HUMAN OTC DRUG LABEL
Date: 20200518

ACTIVE INGREDIENTS: GLYCERIN 6 g/100 g
INACTIVE INGREDIENTS: AVOCADO FRUIT WATER

Direction

nornal skin:Apply 1-2times morning and night

sensitive skin:applu 2-3 times a day

dry skin: apply 4-6times as the skin trouble condition

Caution

when you have any abnormal symptoms or side effects such as red spots swelling or itching after using cosmetics or product.please consult a specialist

dont use in areas with scratches

precautions for storage and handling

Keep out of reach of children

keep away from direct sunlight

INDICATIONS AND USAGE

Naturak mineral ionized water combines with various herbs to enhance nourishment and moisturizing the skin coconut cleansing foam removing impurities and leaving the skin sofen and smooth. Natural fragrance makes you feel relaxed and energized.

Keep out of reach of children

Purpose-Skin Protectant

drug facts

active ingredients-Glycerin 6%

PACKAGE LABEL

NDC:73101-003-01